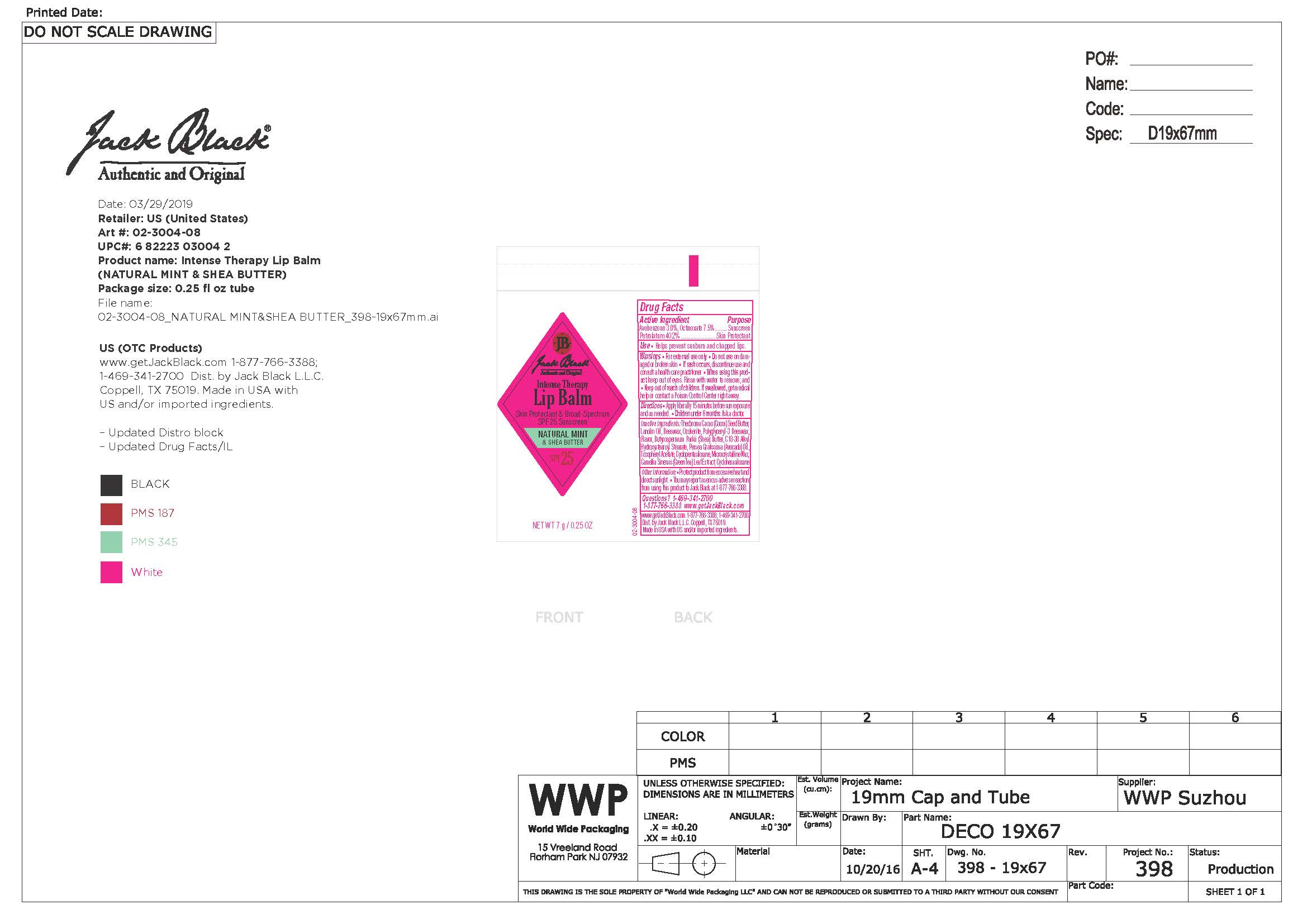 DRUG LABEL: Jack Black Intense Lip Therapy SPF25, Natural Mint and Shea Butter
NDC: 66738-300 | Form: OINTMENT
Manufacturer: Jack Black, LLC
Category: otc | Type: HUMAN OTC DRUG LABEL
Date: 20231109

ACTIVE INGREDIENTS: AVOBENZONE 3 g/1000 g; OCTINOXATE 7.5 g/1000 g; PETROLATUM 40.2 g/1000 g
INACTIVE INGREDIENTS: WHITE WAX; CYCLOMETHICONE 5; CYCLOMETHICONE 6; GREEN TEA LEAF; SHEA BUTTER; LANOLIN OIL; MICROCRYSTALLINE WAX; AVOCADO OIL; COCOA BUTTER; .ALPHA.-TOCOPHEROL ACETATE; CERESIN

Jack Black Intense Lip Therapy SPF25, Natural Mint and Shea Butter

Active Ingredients

Avobenzone 3.0% Sunscreen

Octinoxate 7.5% Sunscreen

Petrolatum 40.2% Sunscreen

Use

Helps prevent sunburn and chapped lips.

Use

Helps prevent sunburn and chapped lips.

Warnings

Stop use if skin rash occurs.

KEEP OUT OF REACH OF CHILDREN

Directions

Apply liberally 15 minutes before sun exposure and as needed. Children under 6 months: ask a doctor.

Inactive Ingredients

Beeswax, Butyrospermum parkii (Shea) Butter, C 18-38 Alkyl Hydroxystearoyl Stearate, Camellia Sinensis (Green tea) Leaf Extract, Cyclohexasiloxane, Cyclopentasiloxane, Flavor, Lanolin, Microcyrstalline Wax, Ozokerite, Persea gratissima (avocado) oil, Polyglyceryl-3 Beeswax, Theobroma cacao (cocoa) See Butter, Tocopheryl Acetate

Questions

1-877-766-3388

www.getjackblack.com